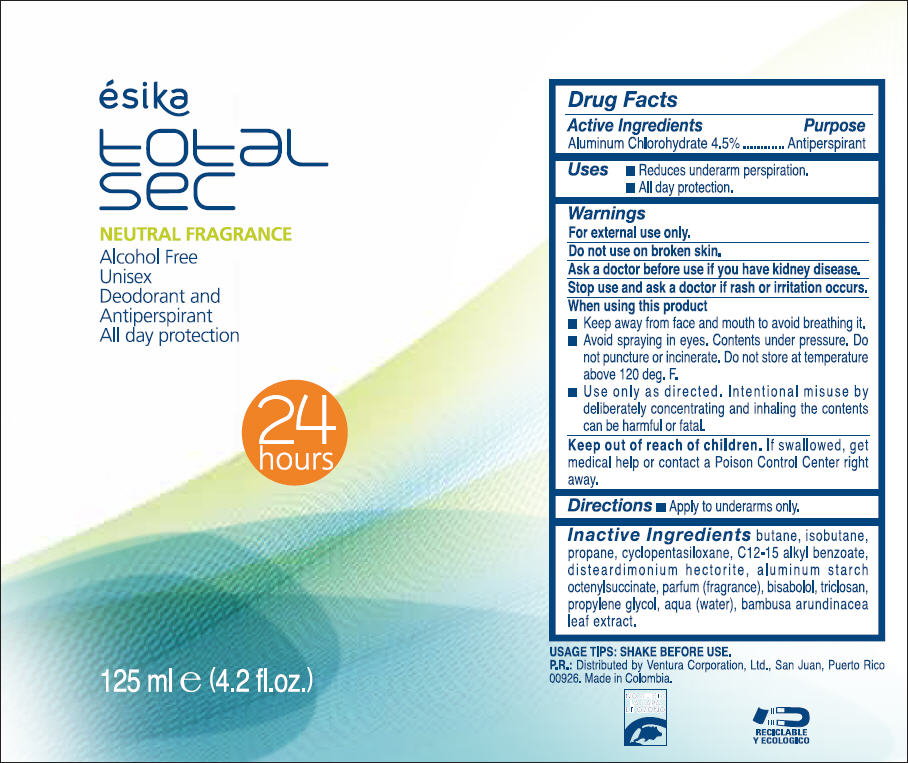 DRUG LABEL: esika 
NDC: 13537-506 | Form: SPRAY
Manufacturer: Ventura Corporation LTD.
Category: otc | Type: HUMAN OTC DRUG LABEL
Date: 20130604

ACTIVE INGREDIENTS: Aluminum Chlorohydrate 0.045 g/1 mL
INACTIVE INGREDIENTS: BUTANE; ISOBUTANE; PROPANE; CYCLOMETHICONE 5; ALKYL (C12-15) BENZOATE; DISTEARDIMONIUM HECTORITE; ALUMINUM STARCH OCTENYLSUCCINATE; LEVOMENOL; TRICLOSAN; PROPYLENE GLYCOL; WATER; BAMBUSA BAMBOS LEAF

ésika
total sec NEUTRAL FRAGRANCE Alcohol Free Unisex Deodorant and Antiperspirant - All day protection

Drug Facts

Active Ingredient

Aluminum Chlorohydrate 4.5%

Purpose

Antiperspirant

Uses

- Reduces underarm perspiration.
- All day protection.

Warnings

For external use only

Do not use on broken skin

Ask a doctor before use if you have kidney disease

Stop use and ask a doctor if rash or irritation occurs

When using this product

- Keep away from face and mouth to avoid breathing it.
- Avoid spraying in eyes. Contents under pressure. Do not puncture or incinerate. Do not store at temperature above 120 deg. F.
- Use only as directed. Intentional misuse by deliberately concentrating and inhaling the contents can be harmful or fatal.

Keep out of reach of children.If swallowed, get medical help or contact a Poison Control Center right away.

Directions

- Apply to underarms only.

Inactive ingredients

BUTANE, ISOBUTANE, PROPANE, CYCLOPENTASILOXANE, C12-15 ALKYL BENZOATE, DISTEARDIMONIUM HECTORITE, ALUMINUM STARCH OCTENYLSUCCINATE, PARFUM (FRAGRANCE), BISABOLOL, TRICLOSAN, PROPYLENE GLYCOL, AQUA (WATER), BAMBUSA ARUNDINACEA LEAF EXTRACT.

P.R.: Distributed by Ventura Corporation, Ltd., San Juan, Puerto Rico 00926.

PRINCIPAL DISPLAY PANEL - 125 mL Bottle Label

ésika

total
sec

NEUTRAL FRAGRANCE

Alcohol Free
Unisex
Deodorant and
Antiperspirant
All day protection

24
hours

125 ml e (4.2 fl.oz.)